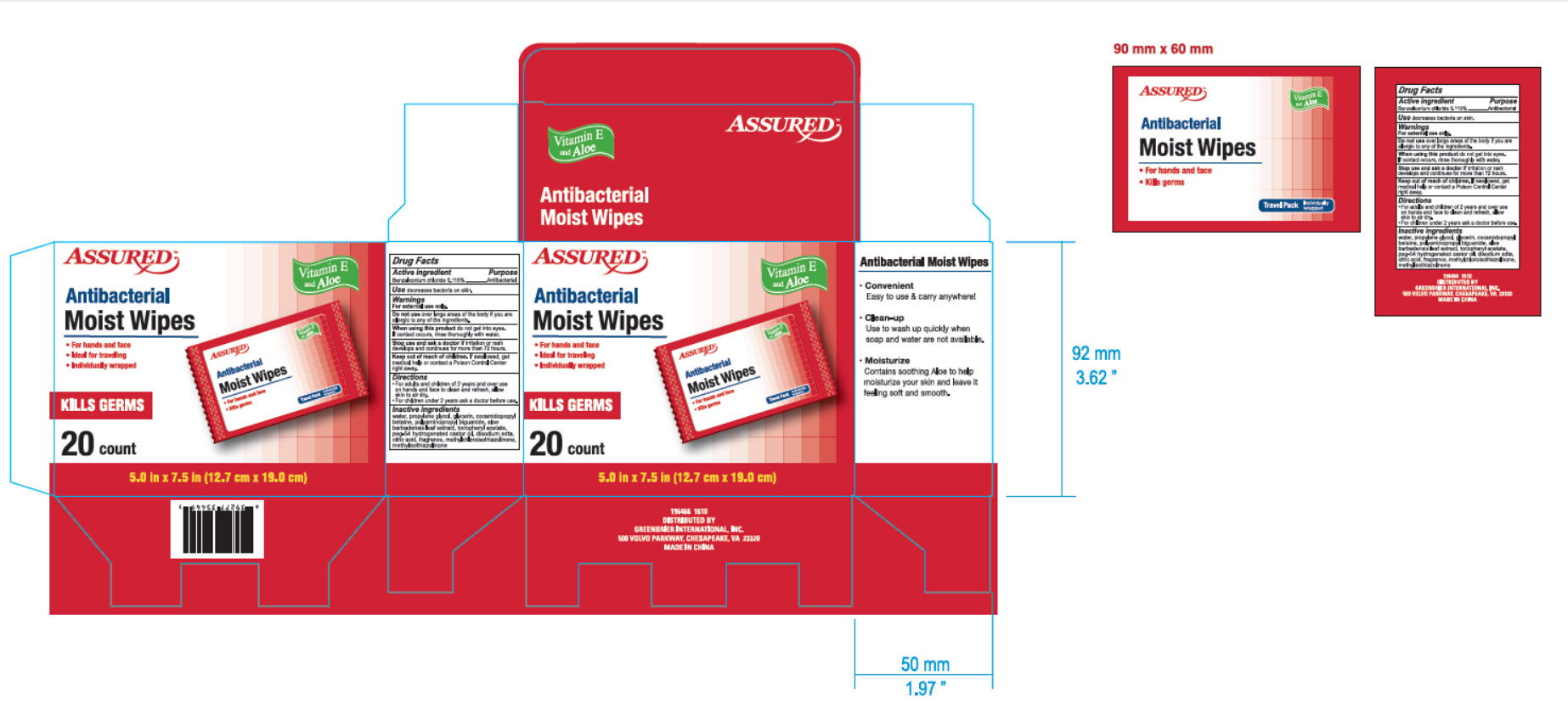 DRUG LABEL: Assured
NDC: 70031-002 | Form: LOTION
Manufacturer: TIANJIN YANSHENG INDUSTRIAL TRADE COMPANY
Category: otc | Type: HUMAN OTC DRUG LABEL
Date: 20160831

ACTIVE INGREDIENTS: BENZALKONIUM CHLORIDE .1 g/100 g
INACTIVE INGREDIENTS: WATER; PROPYLENE GLYCOL; COCAMIDOPROPYL BETAINE; POLYAMINOPROPYL BIGUANIDE; ALOE VERA LEAF; .ALPHA.-TOCOPHEROL ACETATE; PEG-54 HYDROGENATED CASTOR OIL; EDETATE DISODIUM; CITRIC ACID MONOHYDRATE; METHYLCHLOROISOTHIAZOLINONE; METHYL SOYATE

Active ingredient

Benzalkonium chloride 0.115%

Purpose

Antibacterial

INDICATIONS AND USAGE

Use decreases bacteria on skin

Warnings

For external use only

Do not use

-over large areas of the body if you are allergic to any of the ingredients

When using this product avoid contact with eyes and face.

If contact occurs, flush thoroughly with water.

Stop use and ask a doctor if irritation or rash develops and

continues for more than 72 hours

Keep out of reach of children. If swallowed, get medical

help or contact a Poison Control Center right away

Directions

-for adults and children of 2 years and over use

on hands and face to clean and refresh, allow skin to air dry.

-For children under 2 years ask a doctor before using

Inactive ingredient

Water, propylene glycol, glycerin, cocamidopropyl

betaine, polyaminopropyl biguanide, aloe barbadensis leaf extract,

tocopheryl acetate, peg-54 hydrigenated castor oil, disodium edta,

citric acid, fragrance, methylchloroisothiazolinone,

methylsothiazolinone